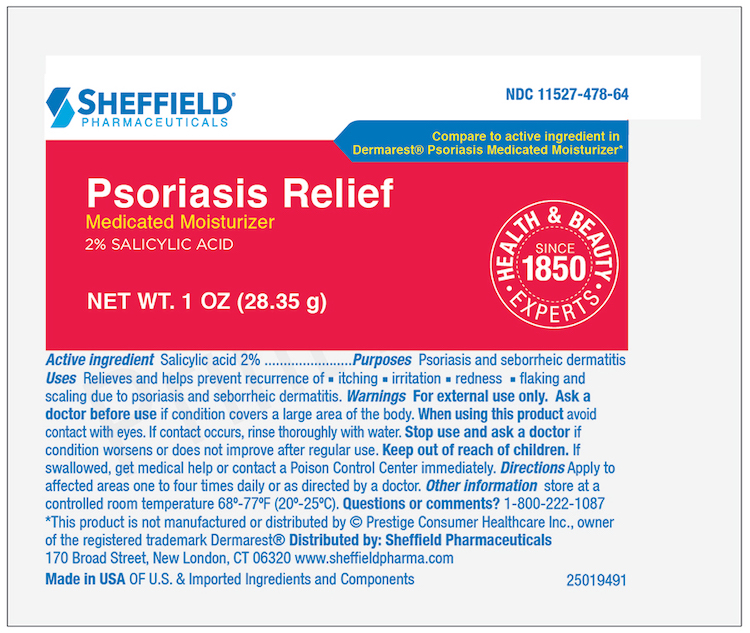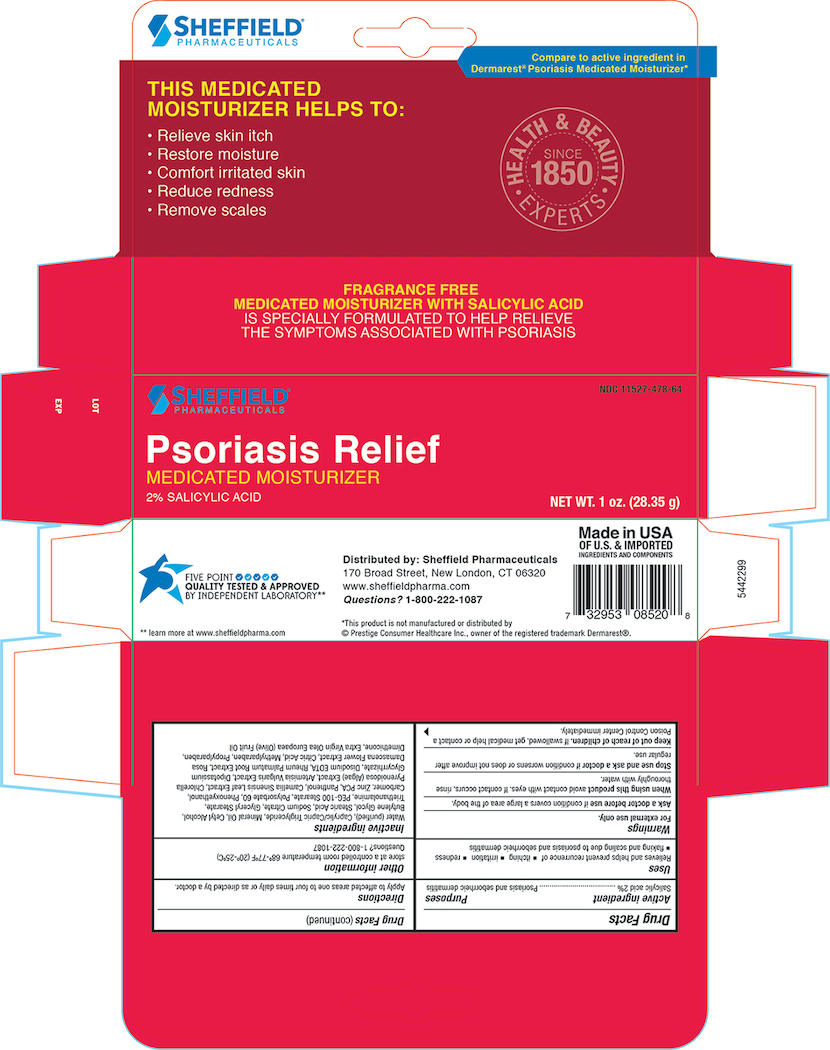 DRUG LABEL: Dr. Sheffield Psoriasis Medicated Moisturizer
NDC: 11527-478 | Form: LOTION
Manufacturer: Sheffield Pharmaceuticals LLC
Category: otc | Type: HUMAN OTC DRUG LABEL
Date: 20231128

ACTIVE INGREDIENTS: SALICYLIC ACID 20 mg/1 g
INACTIVE INGREDIENTS: WATER; MEDIUM-CHAIN TRIGLYCERIDES; MINERAL OIL; CETYL ALCOHOL; BUTYLENE GLYCOL; STEARIC ACID; SODIUM CITRATE; GLYCERYL STEARATE CITRATE; TROLAMINE; PEG-100 STEARATE; POLYSORBATE 60; PHENOXYETHANOL; CARBOMER 934; ZINC PIDOLATE; PANTHENOL; CAMELLIA OLEIFERA LEAF; ARTEMISIA VULGARIS ROOT; GLYCYRRHIZINATE DIPOTASSIUM; EDETATE DISODIUM; METHYLPARABEN; PROPYLPARABEN; RHEUM PALMATUM ROOT; ROSA DAMASCENA FLOWER; CITRIC ACID MONOHYDRATE; DIMETHICONE; OLIVE OIL

Active Ingredient

Salicylic Acid -2%

Purposes

Psoriasis and seborrheic dermatitis

Uses

Relieves and helps prevent recurrence of

- itching
- irration
- redness
- flaking and scaling due to psoriasis and seborrheic dermatitis

Warnings

For external use only

Ask A doctor before use if condition covers a large area of the body.

When using this product avoid contact with eyes. if contact occurs, rinse throughly with water.

Stop use and ask a doctor if condition worsens or does not improve after regular use.

KEEP OUT OF REACH OF CHILDREN

Keep out of the reach of children. If swallowed, get medical help or contact a Poison Control Center immediately.

Directions

Apply to affected areas one to four times daily or as directed by a doctor.

Other information

store at a controlled room temperature 68°-77°F (20°- 25°C)

Questions? 1-800-222-1087

Inactive ingredients

Purifed Water, Caprylic/Capric Triglyceride, Mineral Oil, Cetyl Alcohol, Butylene Glycol, Stearic Acid, Sodium Citrate, Glyceral Stearate, Triethanolamine, PEG-100 Sterate, Polysorbate 60 , Phenoxyethanol, Carbomer, Zinc PCA, Panthenol, Camellia Oleifera leaf extract , Algea Extract, Artemisia Vulgaris Extract, Dipotassium Glycyrrhizate, Disodium EDTA, Rheum Palmatum Extract, Rosa Damascena Extract, Citric Acid, Methylparaben, Propylparaben, Dimethicone, Extra Virign Olea Europaea(Olive) Fruit oil

Principal Display Panel - Carton 1.0 oz

Sheffield Pharmaceuticals NDC 11527-478-64

PSORIASIS

Salicylic Acid 2%

edicated Moisturizer

Made in the USA

NET WT 1 oz. (28g)

Principal Display Panel 1 oz. - Tube

Sheffield Pharmaceuticals NDC 11527-478-64

PSORIASIS

Salicylic Acid 2%

edicated Moisturizer

Made in the USA

NET WT 1 oz. (28g)